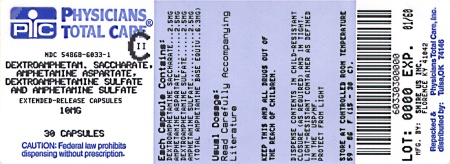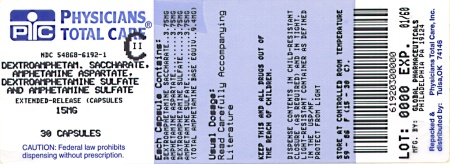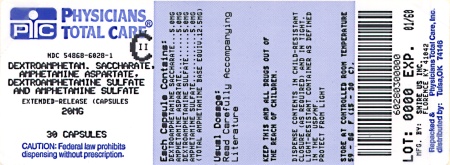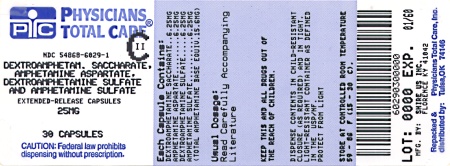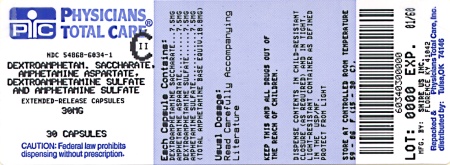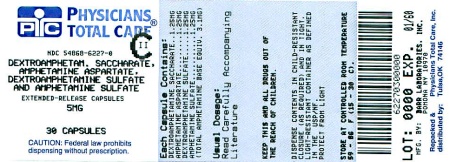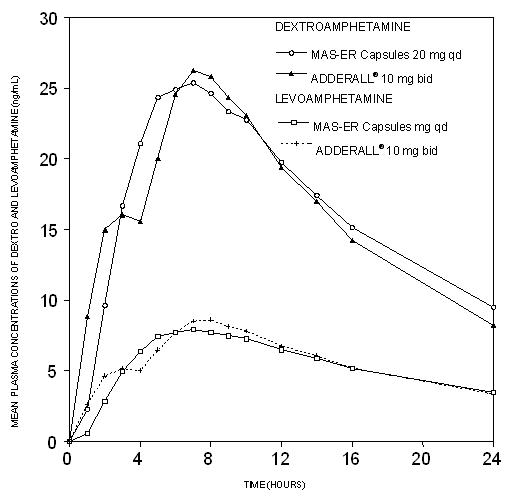 DRUG LABEL: Dextroamphetamine Saccharate, Amphetamine Aspartate, Dextroamphetamine Sulfate and Amphetamine Sulfate
NDC: 54868-6033 | Form: CAPSULE, EXTENDED RELEASE
Manufacturer: Physicians Total Care, Inc.
Category: prescription | Type: HUMAN PRESCRIPTION DRUG LABEL
Date: 20100518
DEA Schedule: CII

ACTIVE INGREDIENTS: DEXTROAMPHETAMINE SULFATE 2.5 mg/1 1; DEXTROAMPHETAMINE SACCHARATE 2.5 mg/1 1; AMPHETAMINE SULFATE 2.5 mg/1 1; AMPHETAMINE ASPARTATE 2.5 mg/1 1
INACTIVE INGREDIENTS: GELATIN; HYPROMELLOSES; METHACRYLIC ACID - METHYL METHACRYLATE COPOLYMER (1:1); SUCROSE; TALC; TRIETHYL CITRATE; TITANIUM DIOXIDE; FD&C BLUE NO. 2

CII
Rx Only

BOXED WARNING

AMPHETAMINES HAVE A HIGH POTENTIAL FOR ABUSE. ADMINISTRATION OF AMPHETAMINES FOR PROLONGED PERIODS OF TIME MAY LEAD TO DRUG DEPENDENCE. PARTICULAR ATTENTION SHOULD BE PAID TO THE POSSIBILITY OF SUBJECTS OBTAINING AMPHETAMINES FOR NON-THERAPEUTIC USE OR DISTRIBUTION TO OTHERS AND THE DRUGS SHOULD BE PRESCRIBED OR DISPENSED SPARINGLY.

MISUSE OF AMPHETAMINE MAY CAUSE SUDDEN DEATH AND SERIOUS CARDIOVASCULAR ADVERSE EVENTS.

DESCRIPTION

Dextroamphetamine Saccharate, Amphetamine Asparate Monohydrate, Dextroamphetamine Sulfate and, Amphetamine Sulfate Extended-Release Capsules is a once daily extended-release, single-entity amphetamine product. Dextroamphetamine Saccharate, Amphetamine Asparate Monohydrate, Dextroamphetamine Sulfate and, Amphetamine Sulfate Extended-Release Capsules combines the neutral sulfate salts of dextroamphetamine and amphetamine, with the dextro isomer of amphetamine saccharate and d,l-amphetamine aspartate monohydrate. The Dextroamphetamine Saccharate, Amphetamine Asparate Monohydrate, Dextroamphetamine Sulfate and, Amphetamine Sulfate Extended-Release Capsules® capsule contains two types of drug-containing beads designed to give a double-pulsed delivery of amphetamines, which prolongs the release of amphetamine from Dextroamphetamine Saccharate, Amphetamine Asparate Monohydrate, Dextroamphetamine Sulfate and, Amphetamine Sulfate Extended-Release Capsules compared to the conventional ADDERALL® (immediate-release) tablet formulation.

EACH CAPSULE CONTAINS: | 5 mg | 10 mg | 15 mg | 20 mg | 25 mg | 30 mg
Dextroamphetamine Saccharate | 1.25 mg | 2.5 mg | 3.75 mg | 5.0 mg | 6.25 mg | 7.5 mg
Amphetamine Aspartate Monohydrate | 1.25 mg | 2.5 mg | 3.75 mg | 5.0 mg | 6.25 mg | 7.5 mg
Dextroamphetamine Sulfate USP | 1.25 mg | 2.5 mg | 3.75 mg | 5.0 mg | 6.25 mg | 7.5 mg
Amphetamine Sulfate USP | 1.25 mg | 2.5 mg | 3.75 mg | 5.0 mg | 6.25 mg | 7.5 mg
Total amphetamine base equivalence | 3.1 mg | 6.3 mg | 9.4 mg | 12.5 mg | 15.6 mg | 18.8 mg

Inactive Ingredients and Colors: The inactive ingredients in Dextroamphetamine Saccharate, Amphetamine Asparate Monohydrate, Dextroamphetamine Sulfate and, Amphetamine Sulfate Extended-Release Capsules capsules include: gelatin capsules, hydroxypropyl methylcellulose, methacrylic acid copolymer, opadry beige, sugar spheres, talc, and triethyl citrate. Gelatin capsules contain edible inks, kosher gelatin, and titanium dioxide. The 5 mg, 10 mg, and 15 mg capsules also contain FD&C Blue #2. The 20 mg, 25 mg, and 30 mg capsules also contain red iron oxide and yellow iron oxide.

CLINICAL PHARMACOLOGY

Pharmacodynamics

Amphetamines are non-catecholamine sympathomimetic amines with CNS stimulant activity. The mode of therapeutic action in Attention Deficit Hyperactivity Disorder (ADHD) is not known. Amphetamines are thought to block the reuptake of norepinephrine and dopamine into the presynaptic neuron and increase the release of these monoamines into the extraneuronal space.

Pharmacokinetics

Pharmacokinetic studies of Dextroamphetamine Saccharate, Amphetamine Asparate Monohydrate, Dextroamphetamine Sulfate and, Amphetamine Sulfate Extended-Release Capsules have been conducted in healthy adult and pediatric (6-12 yrs) subjects, and adolescent (13-17 yrs) and pediatric patients with ADHD. Both ADDERALL® (immediate-release) tablets and Dextroamphetamine Saccharate, Amphetamine Asparate Monohydrate, Dextroamphetamine Sulfate and, Amphetamine Sulfate Extended-Release Capsules contain d-amphetamine and l-amphetamine salts in the ratio of 3:1. Following administration of ADDERALL® (immediate-release), the peak plasma concentrations occurred in about 3 hours for both d-amphetamine and l-amphetamine.

The time to reach maximum plasma concentration (Tmax) for Dextroamphetamine Saccharate, Amphetamine Asparate Monohydrate, Dextroamphetamine Sulfate and, Amphetamine Sulfate Extended-Release Capsules is about 7 hours, which is about 4 hours longer compared to ADDERALL® (immediate-release). This is consistent with the extended-release nature of the product.

Figure 1 Mean d-amphetamine and l-amphetamine plasma concentrations following administration of Dextroamphetamine Saccharate, Amphetamine Asparate Monohydrate, Dextroamphetamine Sulfate and, Amphetamine Sulfate Extended-Release Capsules (MAS-ER) 20 mg (8am) and ADDERALL® (immediate-release) 10 mg bid (8am and 12 noon) in the fed state.

A single dose of Dextroamphetamine Saccharate, Amphetamine Asparate Monohydrate, Dextroamphetamine Sulfate and, Amphetamine Sulfate Extended-Release Capsules 20 mg capsules provided comparable plasma concentration profiles of both d-amphetamine and l-amphetamine to ADDERALL® (immediate-release) 10 mg bid administered 4 hours apart.

The mean elimination half-life for d-amphetamine is 10 hours in adults; 11 hours in adolescents aged 13-17 years and weighing less than or equal to 75 kg/165 lbs; and 9 hours in children aged 6 to 12 years. For the l-amphetamine, the mean elimination half-life in adults is 13 hours; 13 to 14 hours in adolescents; and 11 hours in children aged 6 to 12 years. On a mg/kg body weight basis, children have a higher clearance than adolescents or adults (See Special Populations).

Dextroamphetamine Saccharate, Amphetamine Asparate Monohydrate, Dextroamphetamine Sulfate and, Amphetamine Sulfate Extended-Release Capsules demonstrates linear pharmacokinetics over the dose range of 20 to 60 mg in adults and adolescents weighing greater than 75 kg/165lbs, over the dose range of 10 to 40 mg in adolescents weighing less than or equal to 75 kg/165 lbs, and 5 to 30 mg in children aged 6 to 12 years. There is no unexpected accumulation at steady state in children.

Food does not affect the extent of absorption of d-amphetamine and l-amphetamine, but prolongs Tmax by 2.5 hours (from 5.2 hrs at fasted state to 7.7 hrs after a high-fat meal) for d-amphetamine and 2.1 hours (from 5.6 hrs at fasted state to 7.7 hrs after a high fat meal) for l-amphetamine after administration of Dextroamphetamine Saccharate, Amphetamine Asparate Monohydrate, Dextroamphetamine Sulfate and, Amphetamine Sulfate Extended-Release Capsules 30 mg. Opening the capsule and sprinkling the contents on applesauce results in comparable absorption to the intact capsule taken in the fasted state. Equal doses of Dextroamphetamine Saccharate, Amphetamine Asparate Monohydrate, Dextroamphetamine Sulfate and, Amphetamine Sulfate Extended-Release Capsules strengths are bioequivalent.

Metabolism and Excretion

Amphetamine is reported to be oxidized at the 4 position of the benzene ring to form 4-hydroxyamphetamine, or on the side chain α or β carbons to form alpha-hydroxy-amphetamine or norephedrine, respectively. Norephedrine and 4-hydroxy-amphetamine are both active and each is subsequently oxidized to form 4-hydroxy-norephedrine. Alpha-hydroxy-amphetamine undergoes deamination to form phenylacetone, which ultimately forms benzoic acid and its glucuronide and the glycine conjugate hippuric acid. Although the enzymes involved in amphetamine metabolism have not been clearly defined, CYP2D6 is known to be involved with formation of 4-hydroxy-amphetamine. Since CYP2D6 is genetically polymorphic, population variations in amphetamine metabolism are a possibility.

Amphetamine is known to inhibit monoamine oxidase, whereas the ability of amphetamine and its metabolites to inhibit various P450 isozymes and other enzymes has not been adequately elucidated. In vitro experiments with human microsomes indicate minor inhibition of CYP2D6 by amphetamine and minor inhibition of CYP1A2, 2D6, and 3A4 by one or more metabolites. However, due to the probability of auto-inhibition and the lack of information on the concentration of these metabolites relative to in vivo concentrations, no predications regarding the potential for amphetamine or its metabolites to inhibit the metabolism of other drugs by CYP isozymes in vivo can be made.

With normal urine pHs approximately half of an administered dose of amphetamine is recoverable in urine as derivatives of alpha-hydroxy-amphetamine and approximately another 30%-40% of the dose is recoverable in urine as amphetamine itself. Since amphetamine has a pKa of 9.9, urinary recovery of amphetamine is highly dependent on pH and urine flow rates. Alkaline urine pHs result in less ionization and reduced renal elimination, and acidic pHs and high flow rates result in increased renal elimination with clearances greater than glomerular filtration rates, indicating the involvement of active secretion. Urinary recovery of amphetamine has been reported to range from 1% to 75%, depending on urinary pH, with the remaining fraction of the dose hepatically metabolized. Consequently, both hepatic and renal dysfunction have the potential to inhibit the elimination of amphetamine and result in prolonged exposures. In addition, drugs that effect urinary pH are known to alter the elimination of amphetamine, and any decrease in amphetamine's metabolism that might occur due to drug interactions or genetic polymorphisms is more likely to be clinically significant when renal elimination is decreased, (See PRECAUTIONS).

Special Populations

Comparison of the pharmacokinetics of d- and l-amphetamine after oral administration of Dextroamphetamine Saccharate, Amphetamine Asparate Monohydrate, Dextroamphetamine Sulfate and, Amphetamine Sulfate Extended-Release Capsules in pediatric (6-12 years) and adolescent (13-17 years) ADHD patients and healthy adult volunteers indicates that body weight is the primary determinant of apparent differences in the pharmacokinetics of d- and l-amphetamine across the age range. Systemic exposure measured by area under the curve to infinity (AUC∞) and maximum plasma concentration (Cmax) decreased with increases in body weight, while oral volume of distribution (Vz/F), oral clearance (CL/F), and elimination half-life (t 1/2) increased with increases in body weight.

Pediatric Patients

On a mg/kg weight basis, children eliminated amphetamine faster than adults. The elimination half-life (t1/2) is approximately 1 hour shorter for d-amphetamine and 2 hours shorter for l-amphetamine in children than in adults. However, children had higher systemic exposure to amphetamine (Cmax and AUC) than adults for a given dose of Dextroamphetamine Saccharate, Amphetamine Asparate Monohydrate, Dextroamphetamine Sulfate and, Amphetamine Sulfate Extended-Release Capsules, which was attributed to the higher dose administered to children on a mg/kg body weight basis compared to adults. Upon dose normalization on a mg/kg basis, children showed 30% less systemic exposure compared to adults.

Gender

Systemic exposure to amphetamine was 20-30% higher in women (N=20) than in men (N=20) due to the higher dose administered to women on a mg/kg body weight basis. When the exposure parameters (Cmax and AUC) were normalized by dose (mg/kg), these differences diminished. Age and gender had no direct effect on the pharmacokinetics of d- and l-amphetamine.

Race

Formal pharmacokinetic studies for race have not been conducted. However, amphetamine pharmacokinetics appeared to be comparable among Caucasians (N=33), Blacks (N=8) and Hispanics (N=10).

Clinical Trials

Children

A double-blind, randomized, placebo-controlled, parallel-group study was conducted in children aged 6-12 (N=584) who met DSM-IV® criteria for ADHD (either the combined type or the hyperactive-impulsive type). Patients were randomized to fixed dose treatment groups receiving final doses of 10, 20, or 30 mg of Dextroamphetamine Saccharate, Amphetamine Asparate Monohydrate, Dextroamphetamine Sulfate and, Amphetamine Sulfate Extended-Release Capsules or placebo once daily in the morning for three weeks. Significant improvements in patient behavior, based upon teacher ratings of attention and hyperactivity, were observed for all Dextroamphetamine Saccharate, Amphetamine Asparate Monohydrate, Dextroamphetamine Sulfate and, Amphetamine Sulfate Extended-Release Capsules doses compared to patients who received placebo, for all three weeks, including the first week of treatment, when all Dextroamphetamine Saccharate, Amphetamine Asparate Monohydrate, Dextroamphetamine Sulfate and, Amphetamine Sulfate Extended-Release Capsules subjects were receiving a dose of 10 mg/day. Patients who received Dextroamphetamine Saccharate, Amphetamine Asparate Monohydrate, Dextroamphetamine Sulfate and, Amphetamine Sulfate Extended-Release Capsules showed behavioral improvements in both morning and afternoon assessments compared to patients on placebo.

In a classroom analogue study, patients (N=51) receiving fixed doses of 10 mg, 20 mg or 30 mg Dextroamphetamine Saccharate, Amphetamine Asparate Monohydrate, Dextroamphetamine Sulfate and, Amphetamine Sulfate Extended-Release Capsules demonstrated statistically significant improvements in teacher-rated behavior and performance measures, compared to patients treated with placebo.

Adolescents

A double-blind, randomized, multi-center, parallel-group, placebo-controlled study was conducted in adolescents aged 13-17 (N=327) who met DSM-IV® criteria for ADHD. The primary cohort of patients (n=287, weighing ≤ 75kg/165lbs) was randomized to fixed dose treatment groups and received four weeks of treatment. Patients were randomized to receive final doses of 10 mg, 20 mg, 30 mg, and 40 mg Dextroamphetamine Saccharate, Amphetamine Asparate Monohydrate, Dextroamphetamine Sulfate and, Amphetamine Sulfate Extended-Release Capsules or placebo once daily in the morning; patients randomized to doses greater than 10 mg were titrated to their final doses by 10 mg each week. The secondary cohort consisted of 40 subjects weighing >75kg/165lbs who were randomized to fixed dose treatment groups receiving final doses of 50 mg and 60 mg Dextroamphetamine Saccharate, Amphetamine Asparate Monohydrate, Dextroamphetamine Sulfate and, Amphetamine Sulfate Extended-Release Capsules or placebo once daily in the morning for 4 weeks. The primary efficacy variable was the ADHD-RS-IV total scores for the primary cohort. Improvements in the primary cohort were statistically significantly greater in all four primary cohort active treatment groups (Dextroamphetamine Saccharate, Amphetamine Asparate Monohydrate, Dextroamphetamine Sulfate and, Amphetamine Sulfate Extended-Release Capsules 10 mg, 20 mg, 30 mg, and 40 mg) compared with the placebo group. There was not adequate evidence that doses greater than 20 mg/day conferred additional benefit.

Adults

A double-blind, randomized, placebo-controlled, parallel-group study was conducted in adults (N=255) who met DSM-IV® criteria for ADHD. Patients were randomized to fixed dose treatment groups receiving final doses of 20, 40, or 60 mg of Dextroamphetamine Saccharate, Amphetamine Asparate Monohydrate, Dextroamphetamine Sulfate and, Amphetamine Sulfate Extended-Release Capsules or placebo once daily in the morning for four weeks. Significant improvements, measured with the Attention Deficit Hyperactivity Disorder-Rating Scale (ADHD-RS), an 18- item scale that measures the core symptoms of ADHD, were observed at endpoint for all Dextroamphetamine Saccharate, Amphetamine Asparate Monohydrate, Dextroamphetamine Sulfate and, Amphetamine Sulfate Extended-Release Capsules doses compared to patients who received placebo for all four weeks. There was not adequate evidence that doses greater than 20 mg/day conferred additional benefit.

INDICATIONS

Dextroamphetamine Saccharate, Amphetamine Asparate Monohydrate, Dextroamphetamine Sulfate and, Amphetamine Sulfate Extended-Release Capsules is indicated for the treatment of Attention Deficit Hyperactivity Disorder (ADHD).

The efficacy of Dextroamphetamine Saccharate, Amphetamine Asparate Monohydrate, Dextroamphetamine Sulfate and, Amphetamine Sulfate Extended-Release Capsules in the treatment of ADHD was established on the basis of two controlled trials in children aged 6 to 12, one controlled trial in adolescents aged 13 to 17, and one controlled trial in adults who met DSM-IV® criteria for ADHD (see CLINICAL PHARMACOLOGY), along with extrapolation from the known efficacy of ADDERALL®, the immediate-release formulation of this substance.

A diagnosis of Attention Deficit Hyperactivity Disorder (ADHD; DSM-IV®) implies the presence of hyperactive-impulsive or inattentive symptoms that caused impairment and were present before age 7 years. The symptoms must cause clinically significant impairment, e.g., in social, academic, or occupational functioning, and be present in two or more settings, e.g., school (or work) and at home. The symptoms must not be better accounted for by another mental disorder. For the Inattentive Type, at least six of the following symptoms must have persisted for at least 6 months: lack of attention to details/careless mistakes; lack of sustained attention; poor listener; failure to follow through on tasks; poor organization; avoids tasks requiring sustained mental effort; loses things; easily distracted; forgetful. For the Hyperactive-Impulsive Type, at least six of the following symptoms must have persisted for at least 6 months: fidgeting/squirming; leaving seat; inappropriate running/climbing; difficulty with quiet activities; "on the go;" excessive talking; blurting answers; can't wait turn; intrusive. The Combined Type requires both inattentive and hyperactive-impulsive criteria to be met.

Special Diagnostic Considerations

Specific etiology of this syndrome is unknown, and there is no single diagnostic test. Adequate diagnosis requires the use not only of medical but of special psychological, educational, and social resources. Learning may or may not be impaired. The diagnosis must be based upon a complete history and evaluation of the child and not solely on the presence of the required number of DSM-IV® characteristics.

Need for Comprehensive Treatment Program

Dextroamphetamine Saccharate, Amphetamine Asparate Monohydrate, Dextroamphetamine Sulfate and, Amphetamine Sulfate Extended-Release Capsules is indicated as an integral part of a total treatment program for ADHD that may include other measures (psychological, educational, social) for patients with this syndrome. Drug treatment may not be indicated for all children with this syndrome. Stimulants are not intended for use in the child who exhibits symptoms secondary to environmental factors and/or other primary psychiatric disorders, including psychosis. Appropriate educational placement is essential and psychosocial intervention is often helpful. When remedial measures alone are insufficient, the decision to prescribe stimulant medication will depend upon the physician's assessment of the chronicity and severity of the child's symptoms.

Long-Term Use

The effectiveness of Dextroamphetamine Saccharate, Amphetamine Asparate Monohydrate, Dextroamphetamine Sulfate and, Amphetamine Sulfate Extended-Release Capsules for long-term use, i.e., for more than 3 weeks in children and 4 weeks in adolescents and adults, has not been systematically evaluated in controlled trials. Therefore, the physician who elects to use Dextroamphetamine Saccharate, Amphetamine Asparate Monohydrate, Dextroamphetamine Sulfate and, Amphetamine Sulfate Extended-Release Capsules for extended periods should periodically re-evaluate the long-term usefulness of the drug for the individual patient.

CONTRAINDICATIONS

Advanced arteriosclerosis, symptomatic cardiovascular disease, moderate to severe hypertension, hyperthyroidism, known hypersensitivity or idiosyncrasy to the sympathomimetic amines, glaucoma.

Agitated states.

Patients with a history of drug abuse.

During or within 14 days following the administration of monoamine oxidase inhibitors (hypertensive crises may result).

WARNINGS

Serious Cardiovascular Events

Sudden Death and Pre-existing Structural Cardiac Abnormalities or Other Serious Heart Problems

Children and Adolescents

Sudden death has been reported in association with CNS stimulant treatment at usual doses in children and adolescents with structural cardiac abnormalities or other serious heart problems. Although some serious heart problems alone carry an increased risk of sudden death, stimulant products generally should not be used in children or adolescents with known serious structural cardiac abnormalities, cardiomyopathy, serious heart rhythm abnormalities, or other serious cardiac problems that may place them at increased vulnerability to the sympathomimetic effects of a stimulant drug (see CONTRAINDICATIONS).

Adults

Sudden deaths, stroke, and myocardial infarction have been reported in adults taking stimulant drugs at usual doses for ADHD. Although the role of stimulants in these adult cases is also unknown, adults have a greater likelihood than children of having serious structural cardiac abnormalities, cardiomyopathy, serious heart rhythm abnormalities, coronary artery disease, or other serious cardiac problems. Adults with such abnormalities should also generally not be treated with stimulant drugs (see CONTRAINDICATIONS).

Hypertension and other Cardiovascular Conditions

Stimulant medications cause a modest increase in average blood pressure (about 2-4 mmHg) and average heart rate (about 3-6 bpm) [see ADVERSE EVENTS], and individuals may have larger increases. While the mean changes alone would not be expected to have short-term consequences, all patients should be monitored for larger changes in heart rate and blood pressure. Caution is indicated in treating patients whose underlying medical conditions might be compromised by increases in blood pressure or heart rate, e.g., those with pre-existing hypertension, heart failure, recent myocardial infarction, or ventricular arrhythmia (see CONTRAINDICATIONS).

Assessing Cardiovascular Status in Patients being Treated with Stimulant Medications

Children, adolescents, or adults who are being considered for treatment with stimulant medications should have a careful history (including assessment for a family history of sudden death or ventricular arrhythmia) and physical exam to assess for the presence of cardiac disease, and should receive further cardiac evaluation if findings suggest such disease (e.g. electrocardiogram and echocardiogram). Patients who develop symptoms such as exertional chest pain, unexplained syncope, or other symptoms suggestive of cardiac disease during stimulant treatment should undergo a prompt cardiac evaluation.

Psychiatric Adverse Events

Pre-Existing Psychosis

Administration of stimulants may exacerbate symptoms of behavior disturbance and thought disorder in patients with pre-existing psychotic disorder.

Bipolar Illness

Particular care should be taken in using stimulants to treat ADHD patients with comorbid bipolar disorder because of concern for possible induction of mixed/manic episode in such patients. Prior to initiating treatment with a stimulant, patients with comorbid depressive symptoms should be adequately screened to determine if they are at risk for bipolar disorder; such screening should include a detailed psychiatric history, including a family history of suicide, bipolar disorder, and depression.

Emergence of New Psychotic or Manic Symptoms

Treatment emergent psychotic or manic symptoms, e.g., hallucinations, delusional thinking, or mania in children and adolescents without prior history of psychotic illness or mania can be caused by stimulants at usual doses. If such symptoms occur, consideration should be given to a possible causal role of the stimulant, and discontinuation of treatment may be appropriate. In a pooled analysis of multiple short-term, placebo-controlled studies, such symptoms occurred in about 0.1% (4 patients with events out of 3482 exposed to methylphenidate or amphetamine for several weeks at usual doses) of stimulant-treated patients compared to 0 in placebo-treated patients.

Aggression

Aggressive behavior or hostility is often observed in children and adolescents with ADHD, and has been reported in clinical trials and the postmarketing experience of some medications indicated for the treatment of ADHD. Although there is no systematic evidence that stimulants cause aggressive behavior or hostility, patients beginning treatment for ADHD should be monitored for the appearance of or worsening of aggressive behavior or hostility.

Long-Term Suppression of Growth

Careful follow-up of weight and height in children ages 7 to 10 years who were randomized to either methylphenidate or non-medication treatment groups over 14 months, as well as in naturalistic subgroups of newly methylphenidate-treated and non-medication treated children over 36 months (to the ages of 10 to 13 years), suggests that consistently medicated children (i.e., treatment for 7 days per week throughout the year) have a temporary slowing in growth rate (on average, a total of about 2 cm less growth in height and 2.7 kg less growth in weight over 3 years), without evidence of growth rebound during this period of development. In a controlled trial of Dextroamphetamine Saccharate, Amphetamine Asparate Monohydrate, Dextroamphetamine Sulfate and, Amphetamine Sulfate Extended-Release Capsules in adolescents, mean weight change from baseline within the initial 4 weeks of therapy was –1.1 lbs. and –2.8 lbs., respectively, for patients receiving 10 mg and 20 mg Dextroamphetamine Saccharate, Amphetamine Asparate Monohydrate, Dextroamphetamine Sulfate and, Amphetamine Sulfate Extended-Release Capsules. Higher doses were associated with greater weight loss within the initial 4 weeks of treatment. Published data are inadequate to determine whether chronic use of amphetamines may cause a similar suppression of growth, however, it is anticipated that they will likely have this effect as well. Therefore, growth should be monitored during treatment with stimulants, and patients who are not growing or gaining weight as expected may need to have their treatment interrupted.

Seizures

There is some clinical evidence that stimulants may lower the convulsive threshold in patients with prior history of seizures, in patients with prior EEG abnormalities in the absence of seizures, and very rarely, in patients without a history of seizures and no prior EEG evidence of seizures. In the presence of seizures, the drug should be discontinued.

Visual Disturbance

Difficulties with accommodation and blurring of vision have been reported with stimulant treatment.

PRECAUTIONS

General

The least amount of amphetamine feasible should be prescribed or dispensed at one time in order to minimize the possibility of overdosage. Dextroamphetamine Saccharate, Amphetamine Asparate Monohydrate, Dextroamphetamine Sulfate and, Amphetamine Sulfate Extended-Release Capsules should be used with caution in patients who use other sympathomimetic drugs.

Tics

Amphetamines have been reported to exacerbate motor and phonic tics and Tourette's syndrome. Therefore, clinical evaluation for tics and Tourette's Syndrome in children and their families should precede use of stimulant medications.

Information for Patients

Amphetamines may impair the ability of the patient to engage in potentially hazardous activities such as operating machinery or vehicles; the patient should therefore be cautioned accordingly.

Prescribers or other health professionals should inform patients, their families, and their caregivers about the benefits and risks associated with treatment with amphetamine and should counsel them in its appropriate use. A patient Medication Guide is available for Dextroamphetamine Saccharate, Amphetamine Asparate Monohydrate, Dextroamphetamine Sulfate and, Amphetamine Sulfate Extended-Release Capsules. The prescriber or health professional should instruct patients, their families, and their caregivers to read the Medication Guide and should assist them in understanding its contents. Patients should be given the opportunity to discuss the contents of the Medication Guide and to obtain answers to any questions they may have. The complete text of the Medication Guide is reprinted at the end of this document.

Drug Interactions

Acidifying agents

Gastrointestinal acidifying agents (guanethidine, reserpine, glutamic acid HCl, ascorbic acid, etc.) lower absorption of amphetamines.

Urinary acidifying agents

These agents (ammonium chloride, sodium acid phosphate, etc.) increase the concentration of the ionized species of the amphetamine molecule, thereby increasing urinary excretion. Both groups of agents lower blood levels and efficacy of amphetamines.

Adrenergic blockers

Adrenergic blockers are inhibited by amphetamines.

Alkalinizing agents

Gastrointestinal alkalinizing agents (sodium bicarbonate, etc.) increase absorption of amphetamines. Co-administration of Dextroamphetamine Saccharate, Amphetamine Asparate Monohydrate, Dextroamphetamine Sulfate and, Amphetamine Sulfate Extended-Release Capsules and gastrointestinal alkalinizing agents, such as antacids, should be avoided. Urinary alkalinizing agents (acetazolamide, some thiazides) increase the concentration of the non-ionized species of the amphetamine molecule, thereby decreasing urinary excretion. Both groups of agents increase blood levels and therefore potentiate the actions of amphetamines.

Proton Pump Inhibitors

act on proton pumps by blocking acid production thereby reducing gastric acidity. In the presence of a proton pump inhibitor, the median Tmax of Dextroamphetamine Saccharate, Amphetamine Asparate Monohydrate, Dextroamphetamine Sulfate and, Amphetamine Sulfate Extended-Release Capsules was shortened from 5 hours to 2.75 hours. Therefore, co-administration of Dextroamphetamine Saccharate, Amphetamine Asparate Monohydrate, Dextroamphetamine Sulfate and, Amphetamine Sulfate Extended-Release Capsules and proton pump inhibitors should be avoided.

Antidepressants, tricyclic

Amphetamines may enhance the activity of tricyclic antidepressants or sympathomimetic agents; d-amphetamine with desipramine or protriptyline and possibly other tricyclics cause striking and sustained increases in the concentration of d-amphetamine in the brain; cardiovascular effects can be potentiated.

MAO inhibitors

MAOI antidepressants, as well as a metabolite of furazolidone, slow amphetamine metabolism. This slowing potentiates amphetamines, increasing their effect on the release of norepinephrine and other monoamines from adrenergic nerve endings; this can cause headaches and other signs of hypertensive crisis. A variety of toxic neurological effects and malignant hyperpyrexia can occur, sometimes with fatal results.

Antihistamines

Amphetamines may counteract the sedative effect of antihistamines.

Antihypertensives

Amphetamines may antagonize the hypotensive effects of antihypertensives.

Chlorpromazine

Chlorpromazine blocks dopamine and norepinephrine receptors, thus inhibiting the central stimulant effects of amphetamines, and can be used to treat amphetamine poisoning.

Ethosuximide

Amphetamines may delay intestinal absorption of ethosuximide.

Haloperidol

Haloperidol blocks dopamine receptors, thus inhibiting the central stimulant effects of amphetamines.

Lithium carbonate

The anorectic and stimulatory effects of amphetamines may be inhibited by lithium carbonate.

Meperidine

Amphetamines potentiate the analgesic effect of meperidine.

Methenamine therapy

Urinary excretion of amphetamines is increased, and efficacy is reduced, by acidifying agents used in methenamine therapy.

Norepinephrine

Amphetamines enhance the adrenergic effect of norepinephrine.

Phenobarbital

Amphetamines may delay intestinal absorption of phenobarbital; co-administration of phenobarbital may produce a synergistic anticonvulsant action.

Phenytoin

Amphetamines may delay intestinal absorption of phenytoin; co-administration of phenytoin may produce a synergistic anticonvulsant action.

Propoxyphene

In cases of propoxyphene overdosage, amphetamine CNS stimulation is potentiated and fatal convulsions can occur.

Veratrum alkaloids

Amphetamines inhibit the hypotensive effect of veratrum alkaloids.

Drug/Laboratory Test Interactions

Amphetamines can cause a significant elevation in plasma corticosteroid levels. This increase is greatest in the evening. Amphetamines may interfere with urinary steroid determinations.

Carcinogenesis/Mutagenesis and Impairment of Fertility

No evidence of carcinogenicity was found in studies in which d,l-amphetamine (enantiomer ratio of 1:1) was administered to mice and rats in the diet for 2 years at doses of up to 30 mg/kg/day in male mice, 19 mg/kg/day in female mice, and 5 mg/kg/day in male and female rats. These doses are approximately 2.4, 1.5, and 0.8 times, respectively, the maximum recommended human dose of 30 mg/day [child] on a mg/m ^2 body surface area basis.

Amphetamine, in the enantiomer ratio present in ADDERALL® (immediate-release)(d- to l- ratio of 3:1), was not clastogenic in the mouse bone marrow micronucleus test in vivo and was negative when tested in the E. coli component of the Ames test in vitro. d,l-Amphetamine (1:1 enantiomer ratio) has been reported to produce a positive response in the mouse bone marrow micronucleus test, an equivocal response in the Ames test, and negative responses in the in vitro sister chromatid exchange and chromosomal aberration assays.

Amphetamine, in the enantiomer ratio present in ADDERALL® (immediate-release)(d- to l- ratio of 3:1), did not adversely affect fertility or early embryonic development in the rat at doses of up to 20 mg/kg/day (approximately 5 times the maximum recommended human dose of 30 mg/day on a mg/m^2 body surface area basis).

Pregnancy Pregnancy Category C

Amphetamine, in the enantiomer ratio present in ADDERALL® (d- to l- ratio of 3:1), had no apparent effects on embryofetal morphological development or survival when orally administered to pregnant rats and rabbits throughout the period of organogenesis at doses of up to 6 and 16 mg/kg/day, respectively. These doses are approximately 1.5 and 8 times, respectively, the maximum recommended human dose of 30 mg/day [child] on a mg/m^2 body surface area basis. Fetal malformations and death have been reported in mice following parenteral administration of d-amphetamine doses of 50 mg/kg/day (approximately 6 times that of a human dose of 30 mg/day [child] on a mg/m^2 basis) or greater to pregnant animals. Administration of these doses was also associated with severe maternal toxicity.

A number of studies in rodents indicate that prenatal or early postnatal exposure to amphetamine (d- or d,l-), at doses similar to those used clinically, can result in long-term neurochemical and behavioral alterations. Reported behavioral effects include learning and memory deficits, altered locomotor activity, and changes in sexual function.

There are no adequate and well-controlled studies in pregnant women. There has been one report of severe congenital bony deformity, tracheo-esophageal fistula, and anal atresia (vater association) in a baby born to a woman who took dextroamphetamine sulfate with lovastatin during the first trimester of pregnancy. Amphetamines should be used during pregnancy only if the potential benefit justifies the potential risk to the fetus.

Nonteratogenic Effects

Infants born to mothers dependent on amphetamines have an increased risk of premature delivery and low birth weight. Also, these infants may experience symptoms of withdrawal as demonstrated by dysphoria, including agitation, and significant lassitude.

Usage in Nursing Mothers

Amphetamines are excreted in human milk. Mothers taking amphetamines should be advised to refrain from nursing.

Pediatric Use

Dextroamphetamine Saccharate, Amphetamine Asparate Monohydrate, Dextroamphetamine Sulfate and, Amphetamine Sulfate Extended-Release Capsules is indicated for use in children 6 years of age and older.

Use in Children Under Six Years of Age

Effects of Dextroamphetamine Saccharate, Amphetamine Asparate Monohydrate, Dextroamphetamine Sulfate and, Amphetamine Sulfate Extended-Release Capsules in 3-5 year olds have not been studied. Long-term effects of amphetamines in children have not been well established. Amphetamines are not recommended for use in children under 3 years of age.

Geriatric Use

Dextroamphetamine Saccharate, Amphetamine Asparate Monohydrate, Dextroamphetamine Sulfate and, Amphetamine Sulfate Extended-Release Capsules has not been studied in the geriatric population.

ADVERSE EVENTS

Hypertension

[See WARNINGS section] In a controlled 4-week outpatient clinical study of adolescents with ADHD, isolated systolic blood pressure elevations ≥15 mmHg were observed in 7/64 (11%) placebo-treated patients and 7/100 (7%) patients receiving Dextroamphetamine Saccharate, Amphetamine Asparate Monohydrate, Dextroamphetamine Sulfate and, Amphetamine Sulfate Extended-Release Capsules 10 or 20 mg. Isolated elevations in diastolic blood pressure ≥ 8 mmHg were observed in 16/64 (25%) placebo-treated patients and 22/100 (22%) Dextroamphetamine Saccharate, Amphetamine Asparate Monohydrate, Dextroamphetamine Sulfate and, Amphetamine Sulfate Extended-Release Capsules -treated patients. Similar results were observed at higher doses.

In a single-dose pharmacokinetic study in 23 adolescents, isolated increases in systolic blood pressure (above the upper 95% CI for age, gender, and stature) were observed in 2/17 (12%) and 8/23 (35%), subjects administered 10 mg and 20 mg Dextroamphetamine Saccharate, Amphetamine Asparate Monohydrate, Dextroamphetamine Sulfate and, Amphetamine Sulfate Extended-Release Capsules, respectively. Higher single doses were associated with a greater increase in systolic blood pressure. All increases were transient, appeared maximal at 2 to 4 hours post dose and not associated with symptoms.

The premarketing development program for Dextroamphetamine Saccharate, Amphetamine Asparate Monohydrate, Dextroamphetamine Sulfate and, Amphetamine Sulfate Extended-Release Capsules included exposures in a total of 1315 participants in clinical trials (635 pediatric patients, 350 adolescent patients, 248 adult patients, and 82 healthy adult subjects). Of these, 635 patients (ages 6 to 12) were evaluated in two controlled clinical studies, one open-label clinical study, and two single-dose clinical pharmacology studies (N= 40). Safety data on all patients are included in the discussion that follows. Adverse reactions were assessed by collecting adverse events, results of physical examinations, vital signs, weights, laboratory analyses, and ECGs.

Adverse events during exposure were obtained primarily by general inquiry and recorded by clinical investigators using terminology of their own choosing. Consequently, it is not possible to provide a meaningful estimate of the proportion of individuals experiencing adverse events without first grouping similar types of events into a smaller number of standardized event categories. In the tables and listings that follow, COSTART terminology has been used to classify reported adverse events.

The stated frequencies of adverse events represent the proportion of individuals who experienced, at least once, a treatment-emergent adverse event of the type listed.

Adverse events associated with discontinuation of treatment

In two placebo-controlled studies of up to 5 weeks duration among children with ADHD, 2.4% (10/425) of Dextroamphetamine Saccharate, Amphetamine Asparate Monohydrate, Dextroamphetamine Sulfate and, Amphetamine Sulfate Extended-Release Capsules treated patients discontinued due to adverse events (including 3 patients with loss of appetite, one of whom also reported insomnia) compared to 2.7% (7/259) receiving placebo. The most frequent adverse events associated with discontinuation of Dextroamphetamine Saccharate, Amphetamine Asparate Monohydrate, Dextroamphetamine Sulfate and, Amphetamine Sulfate Extended-Release Capsules in controlled and uncontrolled, multiple-dose clinical trials of pediatric patients (N=595) are presented below. Over half of these patients were exposed to Dextroamphetamine Saccharate, Amphetamine Asparate Monohydrate, Dextroamphetamine Sulfate and, Amphetamine Sulfate Extended-Release Capsules for 12 months or more.

Adverse event | % of pediatric patients discontinuing (n=595)
Anorexia (loss of appetite) | 2.9
Insomnia | 1.5
Weight loss | 1.2
Emotional lability | 1.0
Depression | 0.7

In a separate placebo-controlled 4-week study in adolescents with ADHD, eight patients (3.4%) discontinued treatment due to adverse events among Dextroamphetamine Saccharate, Amphetamine Asparate Monohydrate, Dextroamphetamine Sulfate and, Amphetamine Sulfate Extended-Release Capsules -treated patients (N=233). Three patients discontinued due to insomnia and one patient each for depression, motor tics, headaches, light-headedness, and anxiety.

In one placebo-controlled 4-week study among adults with ADHD, patients who discontinued treatment due to adverse events among Dextroamphetamine Saccharate, Amphetamine Asparate Monohydrate, Dextroamphetamine Sulfate and, Amphetamine Sulfate Extended-Release Capsules -treated patients (N=191) were 3.1% (n=6) for nervousness including anxiety and irritability, 2.6% (n=5) for insomnia, 1% (n=2) each for headache, palpitation, and somnolence; and, 0.5% (n=1) each for ALT increase, agitation, chest pain, cocaine craving, elevated blood pressure, and weight loss.

Adverse events occurring in a controlled trial

Adverse events reported in a 3-week clinical trial of pediatric patients and a 4-week clinical trial in adolescents and adults, respectively, treated with Dextroamphetamine Saccharate, Amphetamine Asparate Monohydrate, Dextroamphetamine Sulfate and, Amphetamine Sulfate Extended-Release Capsules or placebo are presented in the tables below.

The prescriber should be aware that these figures cannot be used to predict the incidence of adverse events in the course of usual medical practice where patient characteristics and other factors differ from those which prevailed in the clinical trials. Similarly, the cited frequencies cannot be compared with figures obtained from other clinical investigations involving different treatments, uses, and investigators. The cited figures, however, do provide the prescribing physician with some basis for estimating the relative contribution of drug and non-drug factors to the adverse event incidence rate in the population studied.

Table 1 Adverse Events Reported by More Than 1% of Pediatric Patients Receiving Dextroamphetamine Saccharate, Amphetamine Asparate Monohydrate, Dextroamphetamine Sulfate and, Amphetamine Sulfate Extended-Release (MAS-ER) Capsules with Higher Incidence Than on Placebo in a 584 Patient Clinical Study
Body System | Preferred Term | MAS-ER (n=374) | Placebo (n=210)
General | Abdominal Pain (stomachache) | 14% | 10%
 | Accidental Injury | 3% | 2%
 | Asthenia (fatigue) | 2% | 0%
 | Fever | 5% | 2%
 | Infection | 4% | 2%
 | Viral Infection | 2% | 0%
Digestive System | Loss of Appetite Diarrhea Dyspepsia Nausea Vomiting | 22% 2% 2% 5% 7% | 2% 1% 1% 3% 4%
Nervous System | Dizziness Emotional Lability Insomnia Nervousness | 2% 9% 17% 6% | 0% 2% 2% 2%
Metabolic/Nutritional | Weight Loss | 4% | 0%

Table 2 Adverse Events Reported by More Than 5% or more of Adolescents Weight less than or equal to 75 kg/165 lbs Receiving Dextroamphetamine Saccharate, Amphetamine Asparate Monohydrate, Dextroamphetamine Sulfate and, Amphetamine Sulfate Extended-Release (MAS-ER) Capsules with Higher Incidence Than Placebo Clinical Forced Weekly-Dose Titration Study*
Body System | Preferred Term | MAS-ER (n=233) | Placebo (n=54)
General | Abdominal Pain (stomachache) | 11% | 2%
Digestive System | Loss of Appetite † | 36% | 2%
Nervous System | Insomnia † Nervousness | 12% 6% | 4% 6%‡
Metabolic/Nutritional | Weight Loss † | 9% | 0%

Note: The following events did not meet the criterion for inclusion in Table 2 but were reported by 2% to 4% of adolescent patients receiving Dextroamphetamine
Saccharate, Amphetamine Asparate Monohydrate, Dextroamphetamine Sulfate and, Amphetamine Sulfate Extended-Release Capsules with a higher incidence than
patients receiving placebo in this study: accidental injury, asthenia (fatigue), dry mouth, dyspepsia, emotional lability, nausea, somnolence, and vomiting.
* Included doses up to 40 mg
† Dose-related adverse events
‡ Appears the same due to rounding

Table 3 Adverse Events Reported by 5% or More of Adults Receiving Dextroamphetamine Saccharate, Amphetamine Asparate Monohydrate, Dextroamphetamine Sulfate and, Amphetamine Sulfate Extended-Release (MAS-ER) Capsules with Higher Incidence Than on Placebo in a 255 Patient Clinical Forced Weekly-Dose Titration Study*
Body System | Preferred Term | MAS-ER (n=191) | Placebo (n=64)
General | Asthenia Headache | 6% 26% | 5% 13%
Digestive System | Loss of Appetite Diarrhea Dry Mouth Nausea | 33% 6% 35% 8% | 3% 0% 5% 3%
Nervous System | Agitation Anxiety Dizziness Insomnia | 8% 8% 7% 27% | 5% 5% 0% 13%
Cardiovascular System | Tachycardia | 6% | 3%
Metabolic/Nutritional | Weight Loss | 11% | 0%
Urogenital System | Urinary Tract Infection | 5% | 0%

Note: The following events did not meet the criterion for inclusion in Table 3 but were reported by 2% to 4% of adult patients receiving Dextroamphetamine Saccharate,
Amphetamine Asparate Monohydrate, Dextroamphetamine Sulfate and, Amphetamine Sulfate Extended-Release Capsules with a higher incidence than patients receiving
placebo in this study: infection, photosensitivity reaction, constipation, tooth disorder, emotional lability, libido decreased, somnolence, speech disorder, palpitation,
twitching, dyspnea, sweating, dysmenorrhea, and impotence.
* Included doses up to 60 mg.

The following adverse reactions have been associated with the use of amphetamine, Dextroamphetamine Saccharate, Amphetamine Asparate Monohydrate, Dextroamphetamine Sulfate and, Amphetamine Sulfate Extended-Release (MAS-ER) Capsules, or ADDERALL®:

Cardiovascular: Palpitations, tachycardia, elevation of blood pressure, sudden death, myocardial infarction. There have been isolated reports of cardiomyopathy associated with chronic amphetamine use.

Central Nervous System: Psychotic episodes at recommended doses, overstimulation, restlessness, dizziness, insomnia, euphoria, dyskinesia, dysphoria, depression, tremor, headache, exacerbation of motor and phonic tics and Tourette's syndrome, seizures, stroke.

Gastrointestinal: Dryness of the mouth, unpleasant taste, diarrhea, constipation, other gastrointestinal disturbances. Anorexia and weight loss may occur as undesirable effects.

Allergic: Urticaria, rash, hypersensitivity reactions including angioedema and anaphylaxis. Serious skin rashes, including Stevens Johnson Syndrome and toxic epidermal necrolysis have been reported.

Endocrine: Impotence, changes in libido.

DRUG ABUSE AND DEPENDENCE

Dextroamphetamine Saccharate, Amphetamine Asparate Monohydrate, Dextroamphetamine Sulfate and, Amphetamine Sulfate Extended-Release (MAS-ER) Capsules is a Schedule II controlled substance.

Amphetamines have been extensively abused. Tolerance, extreme psychological dependence, and severe social disability have occurred. There are reports of patients who have increased the dosage to levels many times higher than recommended. Abrupt cessation following prolonged high dosage administration results in extreme fatigue and mental depression; changes are also noted on the sleep EEG. Manifestations of chronic intoxication with amphetamines may include severe dermatoses, marked insomnia, irritability, hyperactivity, and personality changes. The most severe manifestation of chronic intoxication is psychosis, often clinically indistinguishable from schizophrenia.

OVERDOSAGE

Individual patient response to amphetamines varies widely. Toxic symptoms may occur idiosyncratically at low doses.

Symptoms

Manifestations of acute overdosage with amphetamines include restlessness, tremor, hyperreflexia, rapid respiration, confusion, assaultiveness, hallucinations, panic states, hyperpyrexia and rhabdomyolysis. Fatigue and depression usually follow the central nervous system stimulation. Cardiovascular effects include arrhythmias, hypertension or hypotension and circulatory collapse. Gastrointestinal symptoms include nausea, vomiting, diarrhea, and abdominal cramps. Fatal poisoning is usually preceded by convulsions and coma.

Treatment

Consult with a Certified Poison Control Center for up to date guidance and advice. Management of acute amphetamine intoxication is largely symptomatic and includes gastric lavage, administration of activated charcoal, administration of a cathartic and sedation. Experience with hemodialysis or peritoneal dialysis is inadequate to permit recommendation in this regard. Acidification of the urine increases amphetamine excretion, but is believed to increase risk of acute renal failure if myoglobinuria is present. If acute severe hypertension complicates amphetamine overdosage, administration of intravenous phentolamine has been suggested. However, a gradual drop in blood pressure will usually result when sufficient sedation has been achieved. Chlorpromazine antagonizes the central stimulant effects of amphetamines and can be used to treat amphetamine intoxication.

The prolonged release of mixed amphetamine salts from Dextroamphetamine Saccharate, Amphetamine Asparate Monohydrate, Dextroamphetamine Sulfate and, Amphetamine Sulfate Extended-Release (MAS-ER) Capsules should be considered when treating patients with overdose.

DOSAGE AND ADMINISTRATION

Dosage should be individualized according to the therapeutic needs and response of the patient. Dextroamphetamine Saccharate, Amphetamine Asparate Monohydrate, Dextroamphetamine Sulfate and, Amphetamine Sulfate Extended-Release (MAS-ER) Capsules should be administered at the lowest effective dosage.

Children

In children with ADHD who are 6 years of age and older and are either starting treatment for the first time or switching from another medication, start with 10 mg once daily in the morning; daily dosage may be adjusted in increments of 5 mg or 10 mg at weekly intervals. When in the judgment of the clinician a lower initial dose is appropriate, patients may begin treatment with 5 mg once daily in the morning. The maximum recommended dose for children is 30 mg/day; doses greater than 30 mg/day of Dextroamphetamine Saccharate, Amphetamine Asparate Monohydrate, Dextroamphetamine Sulfate and, Amphetamine Sulfate Extended-Release (MAS-ER) Capsuleshave not been studied in children. Amphetamines are not recommended for children under 3 years of age. Dextroamphetamine Saccharate, Amphetamine Asparate Monohydrate, Dextroamphetamine Sulfate and, Amphetamine Sulfate Extended-Release (MAS-ER) Capsules has not been studied in children under 6 years of age.

Adolescents

The recommended starting dose for adolescents who are 13-17 years of age with ADHD is 10 mg/day. The dose may be increased to 20 mg/day after one week if ADHD symptoms are not adequately controlled.

Adults

In adults with ADHD who are either starting treatment for the first time or switching from another medication, the recommended dose is 20 mg/day.

Patients Currently Using ADDERALL®- Based on bioequivalence data, patients taking divided doses of immediate-release ADDERALL®, for example twice a day, may be switched to Dextroamphetamine Saccharate, Amphetamine Asparate Monohydrate, Dextroamphetamine Sulfate and, Amphetamine Sulfate Extended-Release (MAS-ER) Capsules at the same total daily dose taken once daily. Titrate at weekly intervals to appropriate efficacy and tolerability as indicated.

Dextroamphetamine Saccharate, Amphetamine Asparate Monohydrate, Dextroamphetamine Sulfate and, Amphetamine Sulfate Extended-Release (MAS-ER) Capsules may be taken whole, or the capsule may be opened and the entire contents sprinkled on applesauce. If the patient is using the sprinkle administration method, the sprinkled applesauce should be consumed immediately; it should not be stored. Patients should take the applesauce with sprinkled beads in its entirety without chewing. The dose of a single capsule should not be divided. The contents of the entire capsule should be taken, and patients should not take anything less than one capsule per day.

Dextroamphetamine Saccharate, Amphetamine Asparate Monohydrate, Dextroamphetamine Sulfate and, Amphetamine Sulfate Extended-Release (MAS-ER) Capsules may be taken with or without food.

Dextroamphetamine Saccharate, Amphetamine Asparate Monohydrate, Dextroamphetamine Sulfate and, Amphetamine Sulfate Extended-Release (MAS-ER) Capsules should be given upon awakening. Afternoon doses should be avoided because of the potential for insomnia.

Where possible, drug administration should be interrupted occasionally to determine if there is a recurrence of behavioral symptoms sufficient to require continued therapy.

HOW SUPPLIED

Dextroamphetamine Saccharate, Amphetamine Asparate Monohydrate, Dextroamphetamine Sulfate and, Amphetamine Sulfate Extended-Release (MAS-ER) Capsules are available as:

5 mg- Clear/blue (imprinted M. Amphet Salts 5 mg),

Bottles of 10 | NDC 54868-6227-1
Bottles of 30 | NDC 54868-6227-0

10 mg- Blue/blue (imprinted M. Amphet Salts 10 mg),

Bottles of 10 | NDC 54868-6033-0
Bottles of 30 | NDC 54868-6033-1
Bottles of 90 | NDC 54868-6033-2

15 mg- Blue/white (imprinted M. Amphet Salts 15 mg),

Bottles of 10 | NDC 54868-6192-0
Bottles of 30 | NDC 54868-6192-1

20 mg- Orange/orange (imprinted M. Amphet Salts 20 mg),

Bottles of 10 | NDC 54868-6028-0
Bottles of 30 | NDC 54868-6028-1
Bottles of 60 | NDC 54868-6028-2

25 mg- Orange/white (imprinted M. Amphet Salts 25 mg),

Bottles of 10 | NDC 54868-6029-0
Bottles of 30 | NDC 54868-6029-1
Bottles of 60 | NDC 54868-6029-2

30 mg- Natural/orange (imprinted M. Amphet Salts 30 mg),

Bottles of 10 | NDC 54868-6034-0
Bottles of 30 | NDC 54868-6034-1

Dispense in a tight, light-resistant container as defined in the USP.

Store at 25º C (77º F). Excursions permitted to 15-30º C (59-86º F) [see USP Controlled Room Temperature]

ANIMAL TOXICOLOGY

Acute administration of high doses of amphetamine (d- or d,l-) has been shown to produce long-lasting neurotoxic effects, including irreversible nerve fiber damage, in rodents. The significance of these findings to humans is unknown.

Manufactured for Global Pharmaceuticals, Division of IMPAX Laboratories, Inc.,
Philadelphia, PA 19124 USA
Supplied by Shire LLC, Florence, KY 41042
Made in USA
For more information contact IMPAX Laboratories, Inc., at
1-800-934-6729

Pharmacist: Medication Guide to be dispensed to patients

ADDERALL® is a registered trademark of Shire LLC, under license to Duramed Pharmaceuticals, Inc.

Copyright© 2008, Shire US Inc.

108964
973-01
Rev.10/09

Repackaging and Relabeling by:
Physicians Total Care, Inc.
Tulsa, OK 74146

MEDICATION GUIDE

Dextroamphetamine Saccharate, Amphetamine Asparate Monohydrate, Dextroamphetamine Sulfate and, Amphetamine Sulfate Extended-Release Capsules (mixed salts of a single- entity amphetmanine product)
Read the Medication Guide that comes with Dextroamphetamine Saccharate, Amphetamine Asparate Monohydrate, Dextroamphetamine Sulfate and, Amphetamine Sulfate Extended-Release Capsules before you or your child starts taking it and each time you get a refill. There may be new information. This Medication Guide does not take the place of talking to your doctor about you or your child's treatment with Dextroamphetamine Saccharate, Amphetamine Asparate Monohydrate, Dextroamphetamine Sulfate and, Amphetamine Sulfate Extended-Release Capsules.

What is the most important information I should know about Dextroamphetamine Saccharate, Amphetamine Asparate Monohydrate, Dextroamphetamine Sulfate and, Amphetamine Sulfate Extended-Release Capsules?

Dextroamphetamine Saccharate, Amphetamine Asparate Monohydrate, Dextroamphetamine Sulfate and, Amphetamine Sulfate Extended-Release Capsules is a stimulant medicine. The following have been reported with use of stimulant medicines.

1. Heart-related problems:

- sudden death in patients who have heart problems or heart defects
- stroke and heart attack in adults
- increased blood pressure and heart rate

Tell your doctor if you or your child have any heart problems, heart defects, high blood pressure, or a family history of these problems.

Your doctor should check you or your child carefully for heart problems before starting Dextroamphetamine Saccharate, Amphetamine Asparate Monohydrate, Dextroamphetamine Sulfate and, Amphetamine Sulfate Extended-Release Capsules.

Your doctor should check you or your child's blood pressure and heart rate regularly during treatment with Dextroamphetamine Saccharate, Amphetamine Asparate Monohydrate, Dextroamphetamine Sulfate and, Amphetamine Sulfate Extended-Release Capsules.

Call your doctor right away if you or your child has any signs of heart problems such as chest pain, shortness of breath, or fainting while taking Dextroamphetamine Saccharate, Amphetamine Asparate Monohydrate, Dextroamphetamine Sulfate and, Amphetamine Sulfate Extended-Release Capsules.

2. Mental (Psychiatric) problems:
All Patients

- new or worse behavior and thought problems
- new or worse bipolar illness
- new or worse aggressive behavior or hostility

Children and Teenagers

- new psychotic symptoms (such as hearing voices, believing things that are not true, are suspicious) or new manic symptoms

Tell your doctor about any mental problems you or your child have, or about a family history of suicide, bipolar illness, or depression.

Call your doctor right away if you or your child have any new or worsening mental symptoms or problems while taking Dextroamphetamine Saccharate, Amphetamine Asparate Monohydrate, Dextroamphetamine Sulfate and, Amphetamine Sulfate Extended-Release Capsules, especially seeing or hearing things that are not real, believing things that are not real, or are suspicious.

What Is Dextroamphetamine Saccharate, Amphetamine Asparate Monohydrate, Dextroamphetamine Sulfate and, Amphetamine Sulfate Extended-Release Capsules?

Dextroamphetamine Saccharate, Amphetamine Asparate Monohydrate, Dextroamphetamine Sulfate and, Amphetamine Sulfate Extended-Release Capsules is a once daily central nervous system stimulant prescription medicine. It is used for the treatment of Attention Deficit Hyperactivity Disorder(ADHD). Dextroamphetamine Saccharate, Amphetamine Asparate Monohydrate, Dextroamphetamine Sulfate and, Amphetamine Sulfate Extended-Release Capsules may help increase attention and decrease impulsiveness and hyperactivity in patients with ADHD.

Dextroamphetamine Saccharate, Amphetamine Asparate Monohydrate, Dextroamphetamine Sulfate and, Amphetamine Sulfate Extended-Release Capsules should be used as a part of a total treatment program for ADHD that may include counseling or other therapies.

Dextroamphetamine Saccharate, Amphetamine Asparate Monohydrate, Dextroamphetamine Sulfate and, Amphetamine Sulfate Extended-Release Capsules is a federally controlled substance (CII) because it can be abused or lead to dependence. Keep Dextroamphetamine Saccharate, Amphetamine Asparate Monohydrate, Dextroamphetamine Sulfate and, Amphetamine Sulfate Extended-Release Capsules in a safe place to prevent misuse and abuse. Selling or giving away Dextroamphetamine Saccharate, Amphetamine Asparate Monohydrate, Dextroamphetamine Sulfate and, Amphetamine Sulfate Extended-Release Capsules may harm others, and is against the law.

Tell your doctor if you or your child have (or have a family history of) ever abused or been dependent on alcohol, prescription medicines or street drugs.

Who should not take Dextroamphetamine Saccharate, Amphetamine Asparate Monohydrate, Dextroamphetamine Sulfate and, Amphetamine Sulfate Extended-Release Capsules?

Dextroamphetamine Saccharate, Amphetamine Asparate Monohydrate, Dextroamphetamine Sulfate and, Amphetamine Sulfate Extended-Release Capsules should not be taken if you or your child:

- have heart disease or hardening of the arteries
- have moderate to severe high blood pressure
- have hyperthyroidism
- have an eye problem called glaucoma
- are very anxious, tense, or agitated
- have a history of drug abuse
- are taking or have taken within the past 14 days an anti-depression medicine called a monoamine oxidase inhibitor or MAOI.
- is sensitive to, allergic to, or had a reaction to other stimulant medicines

Dextroamphetamine Saccharate, Amphetamine Asparate Monohydrate, Dextroamphetamine Sulfate and, Amphetamine Sulfate Extended-Release Capsules has not been studied in children less than 6 years old.

Dextroamphetamine Saccharate, Amphetamine Asparate Monohydrate, Dextroamphetamine Sulfate and, Amphetamine Sulfate Extended-Release Capsules is not recommended for use in children less than 3 years old.

Dextroamphetamine Saccharate, Amphetamine Asparate Monohydrate, Dextroamphetamine Sulfate and, Amphetamine Sulfate Extended-Release Capsules may not be right for you or your child. Before starting Dextroamphetamine Saccharate, Amphetamine Asparate Monohydrate, Dextroamphetamine Sulfate and, Amphetamine Sulfate Extended-Release Capsules tell your or your child's doctor about all health conditions (or a family history of) including:

- heart problems, heart defects, or high blood pressure
- mental problems including psychosis, mania, bipolar illness, or depression
- tics or Tourette's syndrome
- liver or kidney problems
- thyroid problems
- seizures or have had an abnormal brain wave test (EEG)

Tell your doctor if you or your child is pregnant, planning to become pregnant, or breastfeeding.

Can Dextroamphetamine Saccharate, Amphetamine Asparate Monohydrate, Dextroamphetamine Sulfate and, Amphetamine Sulfate Extended-Release Capsules be taken with other medicines?

Tell your doctor about all of the medicines that you or your child takes including prescription and non-prescription medicines, vitamins, and herbal supplements. Dextroamphetamine Saccharate, Amphetamine Asparate Monohydrate, Dextroamphetamine Sulfate and, Amphetamine Sulfate Extended-Release Capsules and some medicines may interact with each other and cause serious side effects. Sometimes the doses of other medicines will need to be adjusted while taking Dextroamphetamine Saccharate, Amphetamine Asparate Monohydrate, Dextroamphetamine Sulfate and, Amphetamine Sulfate Extended-Release Capsules.

Your doctor will decide whether Dextroamphetamine Saccharate, Amphetamine Asparate Monohydrate, Dextroamphetamine Sulfate and, Amphetamine Sulfate Extended-Release Capsules can be taken with other medicines.

Especially tell your doctor if you or your child takes:

- anti-depression medicines including MAOIs
- anti-psychotic medicines
- lithium
- narcotic pain medicines
- seizure medicines
- blood thinner medicines
- blood pressure medicines
- stomach acid medicines
- cold or allergy medicines that contain decongestants

Know the medicines that you or your child takes. Keep a list of your medicines with you to show your doctor and pharmacist.

Do not start any new medicine while taking Dextroamphetamine Saccharate, Amphetamine Asparate Monohydrate, Dextroamphetamine Sulfate and, Amphetamine Sulfate Extended-Release Capsules without talking to your doctor first.

How should Dextroamphetamine Saccharate, Amphetamine Asparate Monohydrate, Dextroamphetamine Sulfate and, Amphetamine Sulfate Extended-Release Capsules be taken?

- Take Dextroamphetamine Saccharate, Amphetamine Asparate Monohydrate, Dextroamphetamine Sulfate and, Amphetamine Sulfate Extended-Release Capsules exactly as prescribed. Your doctor may adjust the dose until it is right for you or your child.
- Take Dextroamphetamine Saccharate, Amphetamine Asparate Monohydrate, Dextroamphetamine Sulfate and, Amphetamine Sulfate Extended-Release Capsules once a day in the morning when you first wake up Dextroamphetamine Saccharate, Amphetamine Asparate Monohydrate, Dextroamphetamine Sulfate and, Amphetamine Sulfate Extended-Release Capsules is an extended release capsule. It releases medicine into your body throughout the day.
- Swallow Dextroamphetamine Saccharate, Amphetamine Asparate Monohydrate, Dextroamphetamine Sulfate and, Amphetamine Sulfate Extended-Release Capsules capsules whole with water or other liquids. If you or your child cannot swallow the capsule, open it and sprinkle the medicine over a spoonful of applesauce. Swallow all of the applesauce and medicine mixture without chewing immediately. Follow with a drink of water or other liquid. Never chew or crush the capsule or the medicine inside the capsule.
- Dextroamphetamine Saccharate, Amphetamine Asparate Monohydrate, Dextroamphetamine Sulfate and, Amphetamine Sulfate Extended-Release Capsules can be taken with or without food.
- From time to time, your doctor may stop Dextroamphetamine Saccharate, Amphetamine Asparate Monohydrate, Dextroamphetamine Sulfate and, Amphetamine Sulfate Extended-Release Capsules treatment for a while to check ADHD symptoms.
- Your doctor may do regular checks of the blood, heart, and blood pressure while taking Dextroamphetamine Saccharate, Amphetamine Asparate Monohydrate, Dextroamphetamine Sulfate and, Amphetamine Sulfate Extended-Release Capsules. Children should have their height and weight checked often while taking Dextroamphetamine Saccharate, Amphetamine Asparate Monohydrate, Dextroamphetamine Sulfate and, Amphetamine Sulfate Extended-Release Capsules. Dextroamphetamine Saccharate, Amphetamine Asparate Monohydrate, Dextroamphetamine Sulfate and, Amphetamine Sulfate Extended-Release Capsules treatment may be stopped if a problem is found during these check-ups.
- If you or your child takes too much Dextroamphetamine Saccharate, Amphetamine Asparate Monohydrate, Dextroamphetamine Sulfate and, Amphetamine Sulfate Extended-Release Capsules or overdoses, call your doctor or poison control center right away, or get emergency treatment.

What are possible side effects of Dextroamphetamine Saccharate, Amphetamine Asparate Monohydrate, Dextroamphetamine Sulfate and, Amphetamine Sulfate Extended-Release Capsules?

See "What is the most important information I should know about Dextroamphetamine Saccharate, Amphetamine Asparate Monohydrate, Dextroamphetamine Sulfate and, Amphetamine Sulfate Extended-Release Capsules?" for information on reported heart and mental problems.

Other serious side effects include:

- slowing of growth (height and weight) in children
- seizures, mainly in patients with a history of seizures
- eyesight changes or blurred vision

Common side effects include:

- headache
- decreased appetite
- stomach ache
- nervousness
- trouble sleeping
- mood swings
- weight loss
- dizziness
- dry mouth
- fast heart beat

Dextroamphetamine Saccharate, Amphetamine Asparate Monohydrate, Dextroamphetamine Sulfate and, Amphetamine Sulfate Extended-Release Capsules may affect you or your child's ability to drive or do other dangerous activities.

Talk to your doctor if you or your child has side effects that are bothersome or do not go away.

This is not a complete list of possible side effects. Ask your doctor or pharmacist for more information

Call your doctor for medical advice about side effects. You may report side effects to FDA at 1-800-FDA-1088.

How should I store Dextroamphetamine Saccharate, Amphetamine Asparate Monohydrate, Dextroamphetamine Sulfate and, Amphetamine Sulfate Extended-Release Capsules?

- Store Dextroamphetamine Saccharate, Amphetamine Asparate Monohydrate, Dextroamphetamine Sulfate and, Amphetamine Sulfate Extended-Release Capsules in a safe place at room temperature, 59 to 86° F (15 to 30° C).
- Keep Dextroamphetamine Saccharate, Amphetamine Asparate Monohydrate, Dextroamphetamine Sulfate and, Amphetamine Sulfate Extended-Release Capsules and all medicines out of the reach of children.

General information about Dextroamphetamine Saccharate, Amphetamine Asparate Monohydrate, Dextroamphetamine Sulfate and, Amphetamine Sulfate Extended-Release Capsules

Medicines are sometimes prescribed for purposes other than those listed in a Medication Guide. Do not use Dextroamphetamine Saccharate, Amphetamine Asparate Monohydrate, Dextroamphetamine Sulfate and, Amphetamine Sulfate Extended-Release Capsules for a condition for which it was not prescribed. Do not give Dextroamphetamine Saccharate, Amphetamine Asparate Monohydrate, Dextroamphetamine Sulfate and, Amphetamine Sulfate Extended-Release Capsules to other people, even if they have the same condition. It may harm them and it is against the law.

This Medication Guide summarizes the most important information about Dextroamphetamine Saccharate, Amphetamine Asparate Monohydrate, Dextroamphetamine Sulfate and, Amphetamine Sulfate Extended-Release Capsules. If you would like more information, talk with your doctor. You can ask your doctor or pharmacist for information about Dextroamphetamine Saccharate, Amphetamine Asparate Monohydrate, Dextroamphetamine Sulfate and, Amphetamine Sulfate Extended-Release Capsules that was written for healthcare professionals. For more information, you may also contact IMPAX Laboratories Inc., at 1-800-934-6729.

What are the ingredients in Dextroamphetamine Saccharate, Amphetamine Asparate Monohydrate, Dextroamphetamine Sulfate and, Amphetamine Sulfate Extended-Release Capsules?

Active Ingredients: dextroamphetamine saccharate, amphetamine aspartate monohydrate, dextroamphetamine sulfate, USP, amphetamine sulfate USP

Inactive Ingredients: gelatin capsules, hydroxypropyl methylcellulose, methacrylic acid copolymer, opadry beige, sugar spheres, talc, and triethyl citrate. Gelatin capsules contain edible inks, kosher gelatin, and titanium dioxide. The 5 mg, 10 mg, and 15 mg capsules also contain FD&C Blue #2. The 20 mg, 25 mg, and 30 mg capsules also contain red iron oxide and yellow iron oxide

Manufactured for Global Pharmaceuticals, Division of IMPAX Laboratories, Inc., Philadelphia, PA 19124 USA
Supplied by Shire LLC, Florence, KY 41042
Rev. 10/09
974-01 108964

This Medication Guide has been approved by the U.S. Food and Drug Administration.

PRINCIPAL DISPLAY PANEL

Dextroamphetamine Saccharate,
Amphetamine Aspartate
Monohydrate,
Dextroamphetamine Sulfate
and Amphetamine Sulfate

(Mixed Salts of a Single-Entity
Amphetamine Product)
Extended-Release Capsules

CII

10 mg

Rx only

Dextroamphetamine Saccharate,
Amphetamine Aspartate
Monohydrate,
Dextroamphetamine Sulfate
and Amphetamine Sulfate

(Mixed Salts of a Single-Entity
Amphetamine Product)
Extended-Release Capsules

CII

20 mg

Rx only

Dextroamphetamine Saccharate,
Amphetamine Aspartate
Monohydrate,
Dextroamphetamine Sulfate
and Amphetamine Sulfate

(Mixed Salts of a Single-Entity
Amphetamine Product)
Extended-Release Capsules

CII

25 mg

Rx only

Dextroamphetamine Saccharate,
Amphetamine Aspartate
Monohydrate,
Dextroamphetamine Sulfate
and Amphetamine Sulfate

(Mixed Salts of a Single-Entity
Amphetamine Product)
Extended-Release Capsules

CII

30 mg

Rx only

Dextroamphetamine Saccharate,
Amphetamine Aspartate
Monohydrate,
Dextroamphetamine Sulfate
and Amphetamine Sulfate

(Mixed Salts of a Single-Entity
Amphetamine Product)
Extended-Release Capsules

CII

15 mg

Rx only

Dextroamphetamine Saccharate,
Amphetamine Aspartate
Monohydrate,
Dextroamphetamine Sulfate
and Amphetamine Sulfate

(Mixed Salts of a Single-Entity
Amphetamine Product)
Extended-Release Capsules

CII

5 mg

Rx only